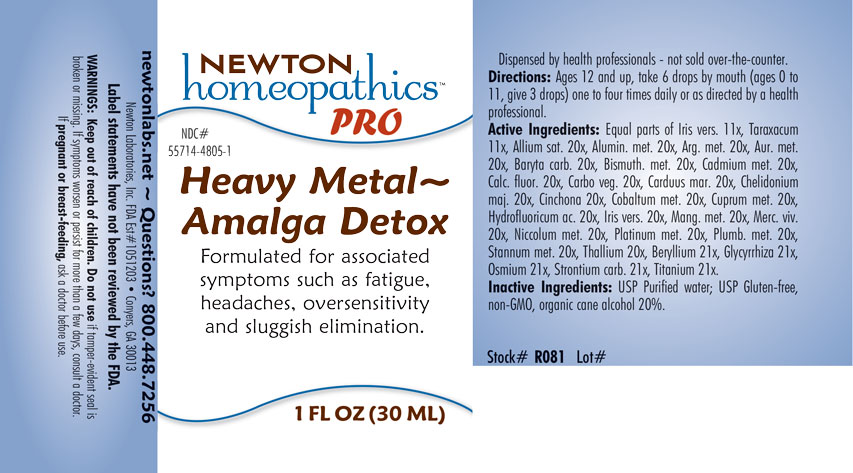 DRUG LABEL: Heavy Metal-Amalga Detox
NDC: 55714-4805 | Form: LIQUID
Manufacturer: Newton Laboratories, Inc.
Category: homeopathic | Type: HUMAN OTC DRUG LABEL
Date: 20201203

ACTIVE INGREDIENTS: GARLIC 20 [hp_X]/1 mL; ALUMINUM 20 [hp_X]/1 mL; SILVER NITRATE 20 [hp_X]/1 mL; GOLD 20 [hp_X]/1 mL; BARIUM CARBONATE 20 [hp_X]/1 mL; BERYLLIUM 21 [hp_X]/1 mL; BISMUTH 20 [hp_X]/1 mL; CADMIUM 20 [hp_X]/1 mL; CALCIUM FLUORIDE 20 [hp_X]/1 mL; ACTIVATED CHARCOAL 20 [hp_X]/1 mL; CHELIDONIUM MAJUS 20 [hp_X]/1 mL; CINCHONA OFFICINALIS BARK 20 [hp_X]/1 mL; COBALT 20 [hp_X]/1 mL; COPPER 20 [hp_X]/1 mL; GLYCYRRHIZA GLABRA 21 [hp_X]/1 mL; HYDROFLUORIC ACID 20 [hp_X]/1 mL; IRIS VERSICOLOR ROOT 20 [hp_X]/1 mL; MANGANESE 20 [hp_X]/1 mL; MERCURY 20 [hp_X]/1 mL; NICKEL 20 [hp_X]/1 mL; OSMIUM 21 [hp_X]/1 mL; PLATINUM 20 [hp_X]/1 mL; LEAD 20 [hp_X]/1 mL; TIN 20 [hp_X]/1 mL; STRONTIUM CARBONATE 21 [hp_X]/1 mL; THALLIUM 20 [hp_X]/1 mL; TITANIUM 21 [hp_X]/1 mL; MILK THISTLE 20 [hp_X]/1 mL; TARAXACUM OFFICINALE 11 [hp_X]/1 mL
INACTIVE INGREDIENTS: ALCOHOL; WATER

Heavy 4805L

INDICATIONS & USAGE SECTION

Formulated for associated symptoms such as fatigue, headaches, oversensitivity and sluggish elimination.

DOSAGE & ADMINISTRATION SECTION

Directions: Ages 12 and up, take 6 drops by mouth (ages 0 to 11, give 3 drops) one to four times daily or as directed by a health professional.

OTC - ACTIVE INGREDIENT SECTION

Equal parts of Iris versicolor 11x, Taraxacum officinale 11x, Allium sativum 20x, Aluminium metallicum 20x, Argentum metallicum 20x, Aurum metallicum 20x, Baryta carbonica 20x, Bismuthum metallicum 20x, Cadmium metallicum 20x, Calcarea fluorica 20x, Carbo vegetabilis 20x, Carduus marianus 11x, Chelidonium majus 20x, Cinchona officinalis 20x, Cobaltum metallicum 20x, Cuprum metallicum 20x, Hydrofluoricum acidum 20x, Iris versicolor 20x, Manganum metallicum 20x, Mercurius vivus 20x, Niccolum metallicum 20x, Platinum metallicum 20x, Plumbum metallicum 20x, Stannum metallicum 20x, Thallium metallicum 20x, Beryllium metallicum 21x, Glycyrrhiza glabra 21x, Osmium metallicum 21x, Strontium carbonicum 21x, Titanium metallicum 21x.

OTC - PURPOSE SECTION

Formulated for associated symptoms such as fatigue, headaches, oversensitivity and sluggish elimination.

INACTIVE INGREDIENT SECTION

Inactive Ingredients: USP Purified Water; USP Gluten-free, non-GMO, organic cane alcohol 20%.

QUESTIONS SECTION

newtonlabs.net – Questions? 800.448.7256

Newton Laboratories, Inc. FDA Est # 1051203 - Conyers, GA 30013

WARNINGS SECTION

WARNINGS: Keep out of reach of children. Do not use if tamper-evident seal is broken or missing. If symptoms worsen or persist for more than a few days, consult a doctor. If pregnant or breast-feeding, ask a doctor before use.

OTC - PREGNANCY OR BREAST FEEDING SECTION

If pregnant or breast-feeding, ask a doctor before use.

OTC - KEEP OUT OF REACH OF CHILDREN SECTION

Keep out of reach of children.